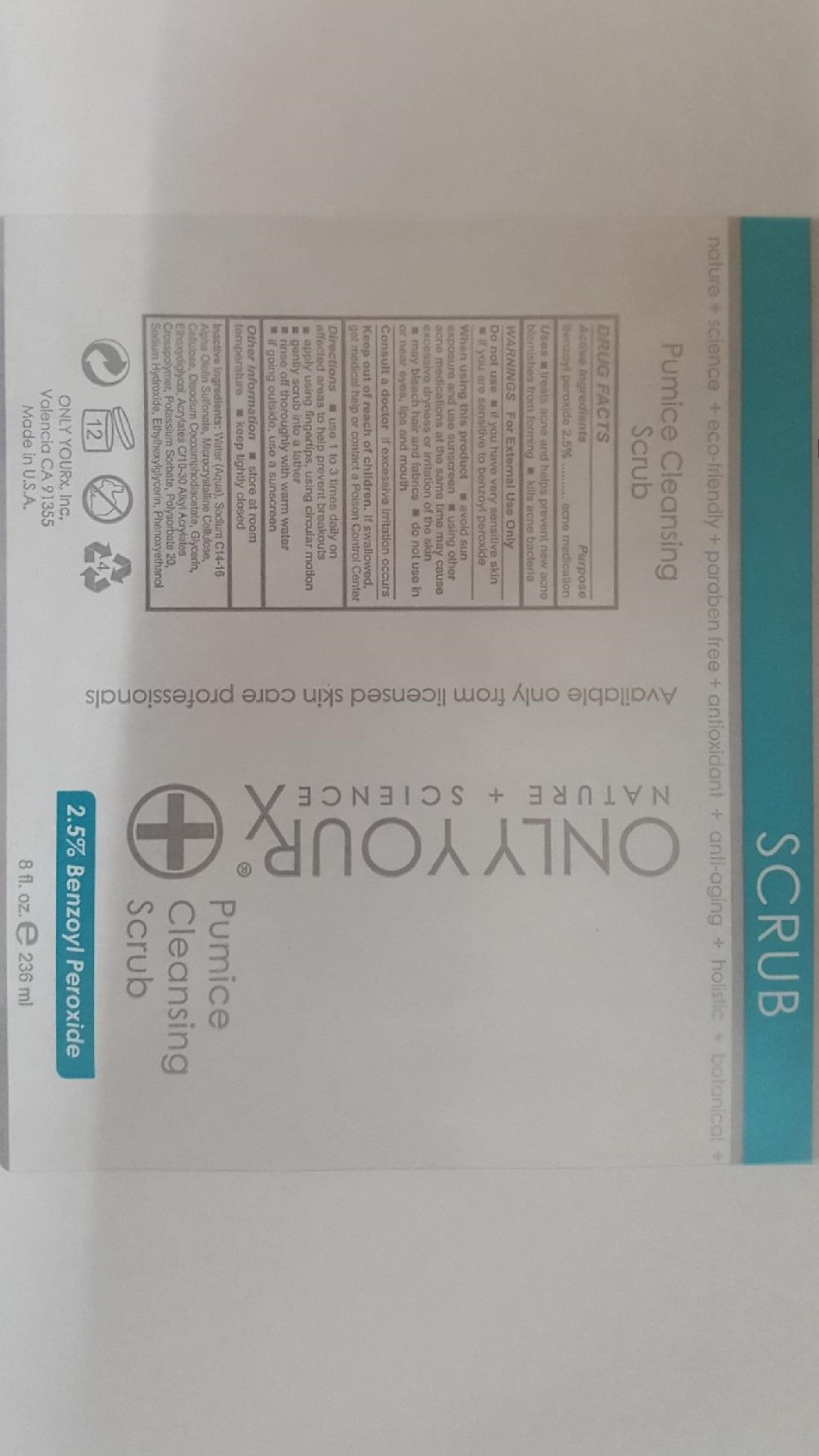 DRUG LABEL: Pumice Cleansing Scrub- 2.5% Benzoyl Peroxide
NDC: 70367-004 | Form: SOAP
Manufacturer: Only Yourx, Inc.
Category: otc | Type: HUMAN OTC DRUG LABEL
Date: 20200123

ACTIVE INGREDIENTS: BENZOYL PEROXIDE 2.5 g/100 mL
INACTIVE INGREDIENTS: SODIUM C14-16 OLEFIN SULFONATE; POLYSORBATE 20; SODIUM HYDROXIDE; ETHYLHEXYLGLYCERIN; PHENOXYETHANOL; ETHOXYDIGLYCOL BEHENATE; GLYCERIN; POTASSIUM SORBATE; DISODIUM COCOAMPHODIACETATE; CELLULOSE, MICROCRYSTALLINE

INACTIVE INGREDIENT

Inactive Ingredients: Water, Sodium C14-16 Alpha Olefin Sulfonate, Microcrystalline Cellulose, Disodium, Cocoamphodiacetate, Glycerin, ethoxydiglycol, Acrylates C10-30 Alkyl Acrylates Crosspolymer, Potassium Sorbate, Polysorbate 20, Sodium Hydroxide, Ethylhexylglycerin, Phenoxyethanol

Active Ingredients: Benzoyl Peroxide 2.5%

Purpose: Acne Medication; a gentle medicated exfoliant wash

INDICATIONS AND USAGE

Uses: Treats acne and helps prevent new acne blemishes from forming, kills acne bacteria

WARNINGS: For External Use Only

Do not use: if you have very sensitive skin; if you are sensitive to benzoyl peroxide

When using this product: avoid sun exposure and use sunscreen; using other acne medications at the same time may cause excessive dryness or irritation of te skin; may bleach hair and fabrics; do not use in or near eyes, lips and mouth

Consult a doctor: if excessive irritation occurs

Keep out of reach of children. If swallowed, get medical help or contact a Poison Control Center

DOSAGE AND ADMINISTRATION

Directions: use 1 to 3 times daily on affected areaws to help prevent breakouts; apply using fingertips, using circular motions; gently scrub into a lather; rinse off thorouhly with warm water; if going outside, use a sunscreen

Other Information: store at room temperature; keep tightly closed